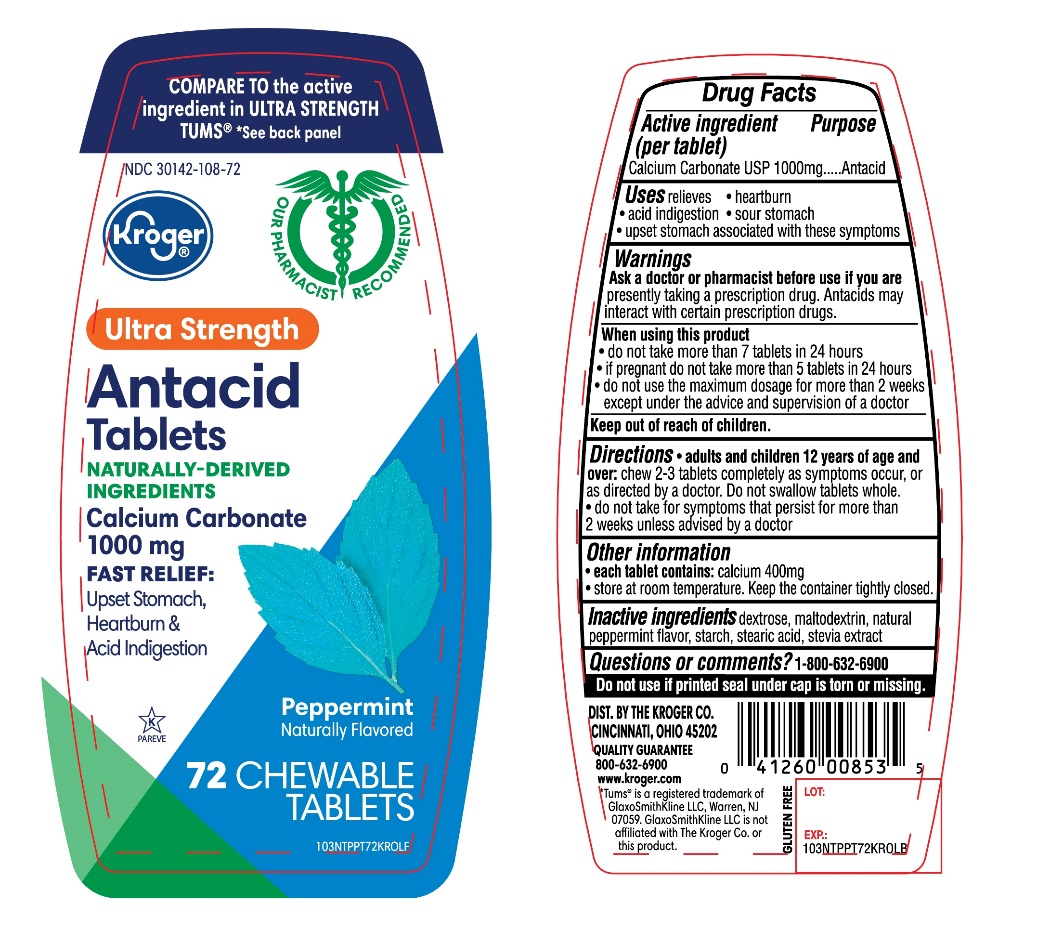 DRUG LABEL: Ultra Strength

NDC: 30142-108 | Form: TABLET, CHEWABLE
Manufacturer: KROGER COMPANY
Category: otc | Type: HUMAN OTC DRUG LABEL
Date: 20250801

ACTIVE INGREDIENTS: CALCIUM CARBONATE 1000 mg/1 1
INACTIVE INGREDIENTS: DEXTROSE, UNSPECIFIED FORM; MALTODEXTRIN; PEPPERMINT; STARCH, CORN; STEARIC ACID; STEVIA REBAUDIANA LEAF

Kroger Ultra Strength 72 Chewable Tablets Drug Facts

Active ingredient (per tablet)

Calcium Carbonate USP 1000mg

Purpose

Antacid

Uses

relieves

- heartburn
- acid indigestion
- sour stomach
- upset stomach associated with these symptoms

Ask a doctor or pharmacist before use if you are

presently taking a prescription drug. Antacids may interact with certain prescription drugs.

When using this product

- do not take more than 7 tablets in 24 hours
- If pregnant do not take more than 5 tablets in 24 hours
- do not use the maximum dosage for more than 2 weeks except under the advice and supervision of a doctor

Directions

- adults and children 12years of age and over:chew 2-3 tablets completely as symptoms occur, or as directed by a doctor. Do not swallow tablets whole.
- do not take for symptoms that persist for more than 2 weeks unless advised by a doctor.

Other information

- each tablets contains:elemental calcium 400mg
- Store at room temperature. Keep the container tightly closed.

Inactive ingredients

dextrose, maltodextrin, natural peppermint flavor, starch, stearic acid, stevia extract.

Questions or comments?

1-866-467-2748

Safety Sealed

Do not use if printed seal under cap is torn or missing.

Package/Label Principal Display Panel

Kroger®

NDC#30142-108-72

COMPARE TO the active ingredient in Ultra Strength TUMS®

*See back panel

Ultra Strength

Antacid Tablets

NATURALLY-DERIVED INGREDIENTS

Calcium Carbonate 1000 mg

FAST RELIEF:Upset Stomach ,Heartburn and Acid Indigestion

Peppermint

Naturally Flavored

GLUTEN FREE

72 CHEWABLE TABLETS

Our Pharmacists Recommend

K PAREVE

DISTRIBUTED BY: THE KROGER CO. CINCINNATI, OHIO 45202

QUALITY GUARANTEE

800-632-6900

www.kroger.com

Tums® is a registered trademark of GlaxoSmithKline LLC, Warren, NJ 07059. GlaxoSmithKline LLC is not affiliated with The Kroger Co. or this product.